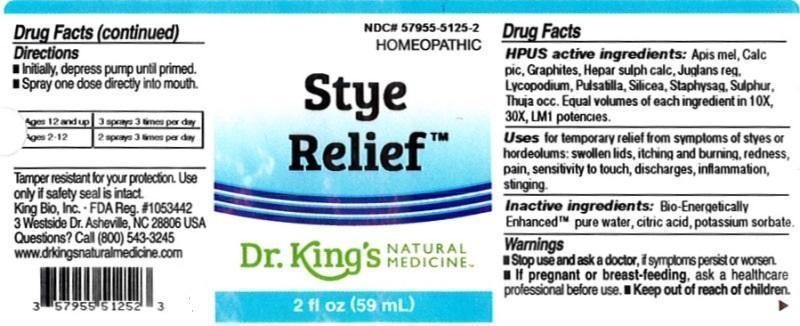 DRUG LABEL: Stye Relief
NDC: 57955-5125 | Form: LIQUID
Manufacturer: King Bio Inc.
Category: homeopathic | Type: HUMAN OTC DRUG LABEL
Date: 20160318

ACTIVE INGREDIENTS: APIS MELLIFERA 10 [hp_X]/59 mL; CALCIUM PICRATE 10 [hp_X]/59 mL; GRAPHITE 10 [hp_X]/59 mL; CALCIUM SULFIDE 10 [hp_X]/59 mL; JUGLANS REGIA FRUIT RIND, IMMATURE 10 [hp_X]/59 mL; LYCOPODIUM CLAVATUM SPORE 10 [hp_X]/59 mL; PULSATILLA VULGARIS 10 [hp_X]/59 mL; SILICON DIOXIDE 10 [hp_X]/59 mL; DELPHINIUM STAPHISAGRIA SEED 10 [hp_X]/59 mL; SULFUR 10 [hp_X]/59 mL; THUJA OCCIDENTALIS LEAFY TWIG 10 [hp_X]/59 mL
INACTIVE INGREDIENTS: WATER; ANHYDROUS CITRIC ACID; POTASSIUM SORBATE

Stye Relief™

ACTIVE INGREDIENT

Drug Facts__________________________________________________________________________________________________________

HPUS active ingredients: Apis mellifica, Calcarea picrata, Graphites, Hepar sulphuris calcareum, Juglans regia, Lycopodium clavatum, Pulsatilla, Silicea, Staphysagria, Sulphur, Thuja occidentalis. Equal volumes of each ingredient in 10X, 30X, and LM1 potencies.

INDICATIONS AND USAGE

Uses for temporary relief from symptoms of styes or hordeolums: swollen lids, itching and burning, redness, pain, sensitivity to touch, discharges, inflammation, and stinging.

Inactive Ingredients:

Bio-Energetically Enhanced™ pure water, citric acid and potassium sorbate.

Warnings

- Stop use and ask your doctor if symptoms persist or worsen.
- If pregnant or breast-feeding, ask a healthcare professional before ues.

- Keep out of reach of children.

Directions

- Initially, depress pump until primed.
- Spray one dose directly into mouth.
- Ages 12 and up: 3 sprays 3 times per day.
- Ages 2-12 years: 2 sprays 3 times per day.

OTHER SAFETY INFORMATION

Tamper resistant for your protection. Use only if safety seal is intact.

PURPOSE

Uses for temporary relief from symptoms of styes or hordeolums:

- swollen lids
- itching and burning
- redness
- pain
- sensitivity to touch
- discharges
- inflammation
- stinging